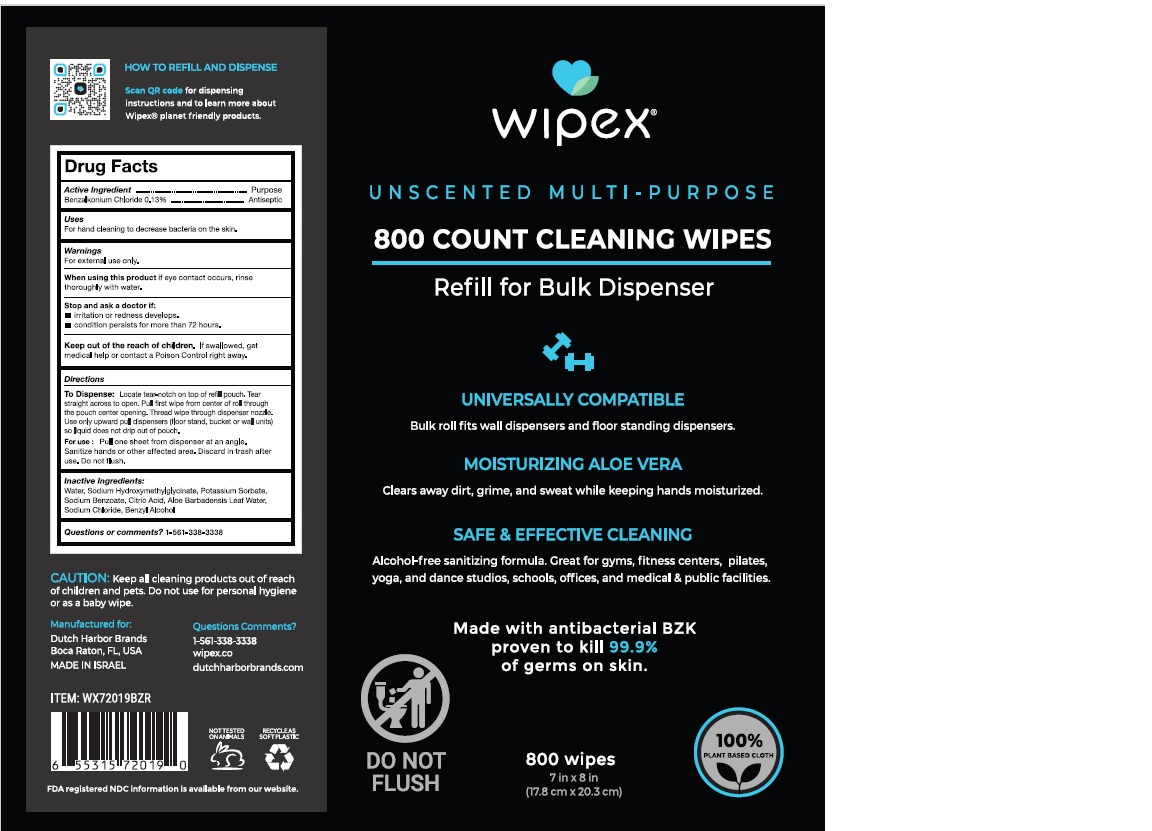 DRUG LABEL: Wipex
NDC: 74680-201 | Form: CLOTH
Manufacturer: Unico International Trading Corporation
Category: otc | Type: HUMAN OTC DRUG LABEL
Date: 20260108

ACTIVE INGREDIENTS: BENZALKONIUM CHLORIDE 1.3 mg/1 mL
INACTIVE INGREDIENTS: POTASSIUM SORBATE; SODIUM BENZOATE; CITRIC ACID MONOHYDRATE; ALOE VERA LEAF; SODIUM HYDROXYMETHYLGLYCINATE; WATER; SODIUM CHLORIDE

Active Ingredient

Benzalkonium chloride

Keep our of the reach of children

Keep out of the reach of children, except with adult supervision.

Warnings

For external use only. Do not use in the eyes. In case of eye contact, rinse with water. If irritation develops, discontinue use. Consult a doctor if irritation continues for more than 72 hours. If swallowed seek medical attention or call a poison control center.

Inactive ingredients

Aqua, Decyl Glucoside, Glycerin, Sodium Hydroxymethylglycinate, Citric Acid, PEG-12 Dimethicone Copolyol, Tetrasodium EDTA, Potassium Sorbate, Sodium Benzoate, Aloe Barbadensis Leaf Extract, Charmomilla Recutita (Matricaria),Flower Extract, Allantoin, Panthenol, Tocopheryl Acetate

Purpose

Antibacterial

To dispense

Locate tear-notch on top of refill pouch. Tear straight across to open. Pull first wipe from center of roll through the pouch center opening. Thread wipe through dispenser nozzle. Use only upward pull dispensers.

To use

Sanitize hands or other affected area. Discard in trash after use.